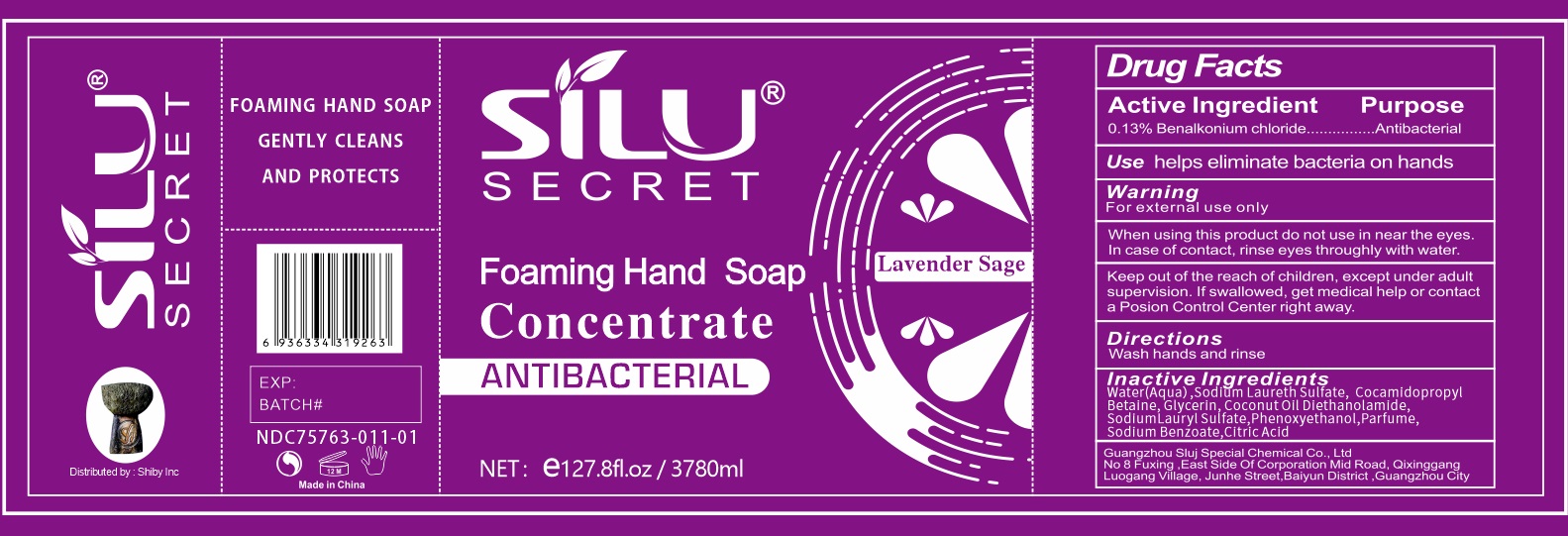 DRUG LABEL: Foaming Hand
NDC: 82110-001 | Form: LIQUID
Manufacturer: SHIBY INC
Category: otc | Type: HUMAN OTC DRUG LABEL
Date: 20230223

ACTIVE INGREDIENTS: BENZALKONIUM CHLORIDE 1.3 mg/1 mL
INACTIVE INGREDIENTS: WATER; SODIUM LAURETH SULFATE; COCAMIDOPROPYL BETAINE; GLYCERIN; COCO DIETHANOLAMIDE; SODIUM LAURYL SULFATE; PHENOXYETHANOL; SODIUM BENZOATE; CITRIC ACID MONOHYDRATE

Foaming Hand Soap

Active Ingredient

0.13% Benalkonium chloride

Purpose

Antibacterial

Use

helps eliminate bacteria on hands

Warning

For external use only

When using this product

do not use in near the eyes. In case of contact, rinse eyes thoroughly with water.

Keep out of reach of children,

except under adult supervision. If swallowed, get medical help or contact a Poison Control Center right away.

Directions

Wash hands and rinse

Inactive Ingredients

Water (Aqua), Sodium Laureth Sulfate, Cocamidopropyl Betaine, Glycerin, Coconut Oil Diethanolamide, Sodium Lauryl Sulfate, Phenoxyethanol, Parfume, Sodium Benzoate, Citric Acid